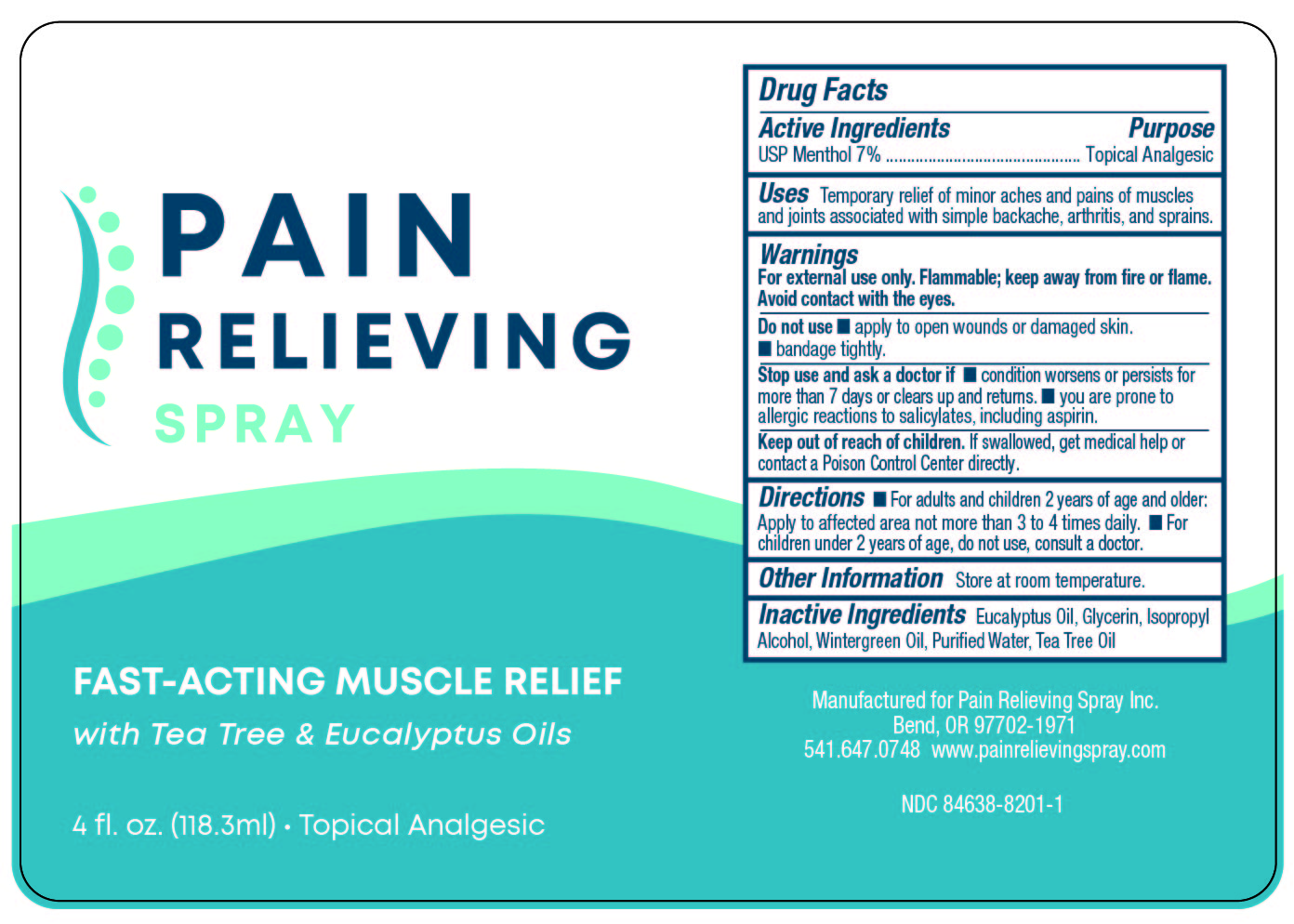 DRUG LABEL: Pain Relief
NDC: 84638-8201 | Form: AEROSOL, SPRAY
Manufacturer: Pain Relieving Spray Inc.
Category: otc | Type: HUMAN OTC DRUG LABEL
Date: 20240809

ACTIVE INGREDIENTS: MENTHOL 70 mg/1 L
INACTIVE INGREDIENTS: EUCALYPTUS OIL; COCONUT OIL; WATER; GLYCERIN; ISOPROPYL ALCOHOL; METHYL SALICYLATE; PEPPERMINT OIL

Dr. Tobey's Pain Relieving Spray

Active Ingredients

USP Menthol 7%

Purpose

Topical Analgesic

Uses

Temporary relief of minor aches and pains of muscles and joints.

Warning

For external use only.

Flammable

Keep away from flame.

Keep out of reach of children.

If swallowed get medical help or contact a poison control center right away. Avoid contact with eyes.

DO NOT USE

Do not apply to open wounds or damaged skin. Do not bandage tightly.

ASK DOCTOR

Consult a doctor if excessive skin irritation occurs, or if you are prone to allergic reactions to salicylates,including aspirin. If condition worsens, if symptoms persist for more than 7 days or clear up and recur again within a few days, discontinue use of this product and consult a doctor.

Directions

For adults and children 2 years of age and older: Shake well and apply to affected area not more than 3-4 times daily. Will not stain clothing. For children under 2 years of age, consult a doctor.

Other Information

Store at room temperature.

Inactive Ingredients

Pain Relieving Spray, 4oz (118.3ml) . Topical Analgesic

Water, Isopropyl Alcohol, Glycerol, Eucalyptus Leaf Oil, Wintergreen Leaf Oil, Peppermint Oil, Coconut Oil.

Labeling

Pain Relieving Spray, 4fl.oz. (118.3mL0, Topical Analgesic
Menthol 7%,
Eucalyptus Oil, Glycerin, Isopropyl Alcohol, Wintergreen Oil, Purified Water, Tea Tree Oil
Pain Relieving Spray Inc., Bend, OR 97702-1971